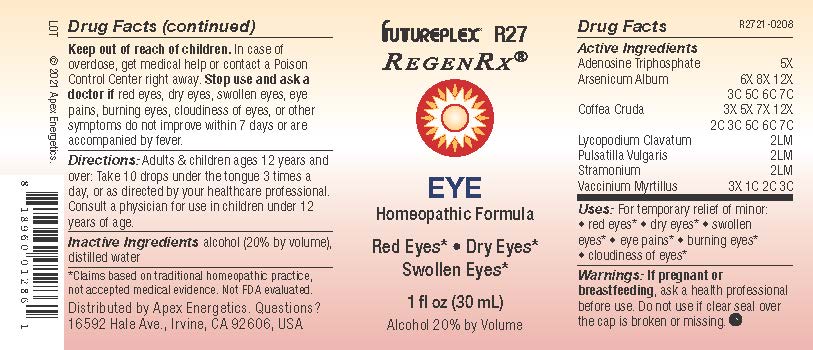 DRUG LABEL: R27
NDC: 63479-1827 | Form: SOLUTION/ DROPS
Manufacturer: Apex Energetics Inc.
Category: homeopathic | Type: HUMAN OTC DRUG LABEL
Date: 20240108

ACTIVE INGREDIENTS: ARSENIC TRIOXIDE 7 [hp_C]/1 mL; ARABICA COFFEE BEAN 7 [hp_C]/1 mL; LYCOPODIUM CLAVATUM SPORE 2 [hp_Q]/1 mL; PULSATILLA VULGARIS 2 [hp_Q]/1 mL; ADENOSINE TRIPHOSPHATE 5 [hp_X]/1 mL; DATURA STRAMONIUM 2 [hp_Q]/1 mL; BILBERRY 3 [hp_C]/1 mL
INACTIVE INGREDIENTS: WATER; ALCOHOL

R27

Active Ingredients
Adenosine Triphosphate | 5X
Arsenicum Album | 6X 8X 12X 3C 5C 6C 7C
Coffea Cruda | 3X 5X 7X 12X 2C 3C 5C 6C 7C
Lycopodium Clavatum | 2LM
Pulsatilla Vulgaris | 2LM
Stramonium | 2LM
Vaccinium Myrtillus | 3X 1C 2C 3C

INDICATIONS AND USAGE

Uses:

For temporary relief of minor:

red eyes*

dry eyes*

swollen eyes*

eye pains*

burning eyes*

cloudiness of eyes*

*Claims based on traditional homeopathic practice, not accepted medical evidence. Not FDA evaluated.

Warnings:

PREGNANCY OR BREAST FEEDING

If pregnant or breastfeeding, ask a health professional before use.

Do not use if clear seal over the cap is broken or missing.

Keep out of reach of children. In case of overdose, get medical help or contact a Poison Control Center right away.

Stop use and ask a doctor if red eyes, dry eyes, swollen eyes, eye pains, burning eyes, cloudiness of eyes, or other symptoms do not improve within 7 days or are accompanied by fever.

DOSAGE AND ADMINISTRATION

Adults & children ages 12 years and over: Take 10 drops under the tongue 3 times a day, or as directed by your healthcare professional. Consult a physician for use in children under 12 years of age.

INACTIVE INGREDIENT

alcohol (20% by volume), distilled water

Distributed by Apex Energetics. Questions?

16592 Hale Ave., Irvine, CA 92606, USA

PACKAGE LABEL

FUTUREPLEX® R27

REGENRX®

EYE

Homeopathic Formula

Red Eyes*

Dry Eyes*

Swollen Eyes*

1 fl oz (30 mL)

Alcohol 20% by Volume